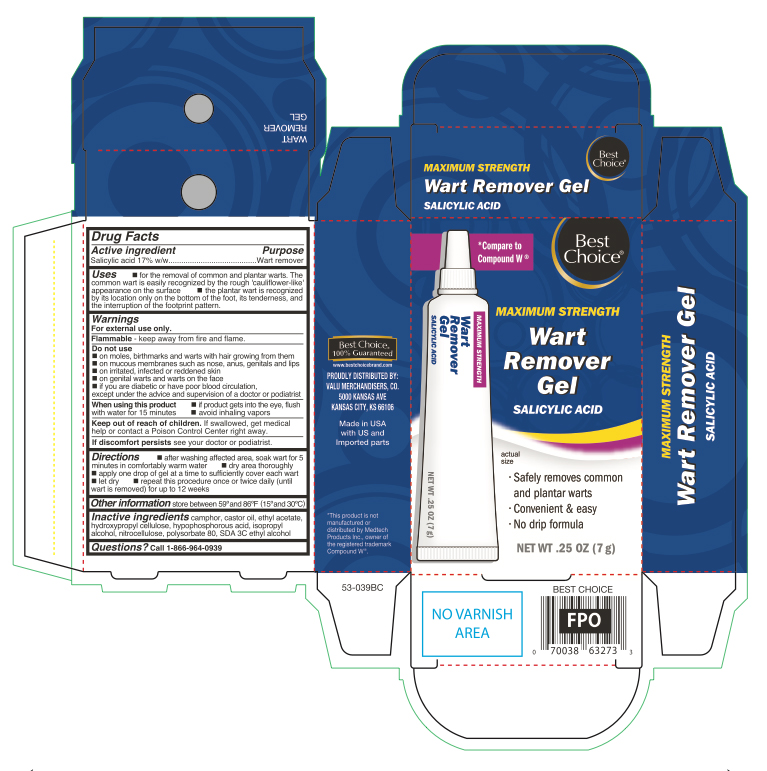 DRUG LABEL: Salicylic Acid
NDC: 63941-553 | Form: GEL
Manufacturer: VALU MERCHANDISERS, CO
Category: otc | Type: HUMAN OTC DRUG LABEL
Date: 20251124

ACTIVE INGREDIENTS: SALICYLIC ACID 0.17 g/7 g
INACTIVE INGREDIENTS: CAMPHOR (NATURAL); ALCOHOL; ETHYL ACETATE; HYPOPHOSPHOROUS ACID; HYDROXYPROPYL CELLULOSE (1600000 WAMW); POLYSORBATE 80; PYROXYLIN; CASTOR OIL

Best Choice Wart Remover Gel Tube

Active ingredient

Salicylic acid 17%w/w

Purpose

Wart remover

Uses

- for the removal of common and plantar warts. The common wart is easily recognized by the rough 'cauliflower-like' appearance of the surface.
- Plantar wart is recognized by its location only on the bottom of the foot, its tenderness and the interruption of the footprint pattern.

Warnings

For external use only.

Flammable

keep away from fire and flame

Do not use

- on moles, birth marks and warts with hair growing from them
- on mucous membranes such as nose, anus, genitals and lips
- on irritated, infected or reddened skin
- on genital warts and warts on the face
- if you are diabetic or have poor blood circulation, except under the advice and supervision of a doctor or podiatrist

When using this product

- if product gets into the eyes, flush with water for 15 minutes
- avoid inhaling vapors

Keep out of reach of children.

If swallowed, get medical help or contact a Poison Control Center right away.

if discomfort persists

see your doctor or podiatrist.

Directions

- after washing affected area, soak wart in for 5 minutes in comfortably warm water
- dry area thoroughly
- apply one drop of gel at a time to sufficiently cover each wart
- let dry
- repeat this procedure once or twice daily (until wart is removed) for up to 12 weeks

Other information

store between 59°F to 86°F (15°C to 30°C)

Inactive ingredients

camphor, castor oil, ethyl acetate, hydroxypropyl cellulose, hypophosphorous acid, isopropyl alcohol, nitrocellulose, polysorbate 80, SDA 3C ethyl alcohol

Questions?

call 1-866-964-0939

Principal Display Panel

Best

Choice

MAXIMUM STRENGTH

Wart

Remover

Gel

SALICYLIC ACID

- Safety removes common and plantar warts
- Convenient & easy
- No drip formula

NET WT .25 OZ (7 g)